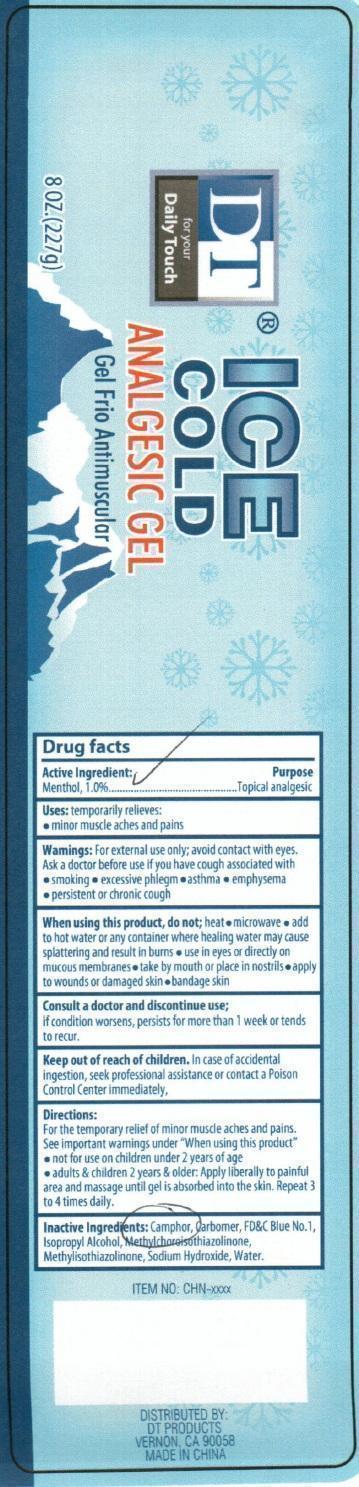 DRUG LABEL: DT Ice Cold Analgesic
NDC: 50523-000 | Form: GEL
Manufacturer: Volume Distributors, Inc.
Category: otc | Type: HUMAN OTC DRUG LABEL
Date: 20150803

ACTIVE INGREDIENTS: MENTHOL 1 g/100 g
INACTIVE INGREDIENTS: CAMPHOR (SYNTHETIC); FD&C BLUE NO. 1; ISOPROPYL ALCOHOL; METHYLCHLOROISOTHIAZOLINONE; METHYLISOTHIAZOLINONE; SODIUM HYDROXIDE; WATER

DT Ice Cold Analgesic Gel

DRUG FACTS

Active ingredients Purpose

Menthol (1%)................................Topical Analgesic

Purpose
topical analgesic

Uses-

temporarily relieves:minor muscle aches and pains

Warnings

For external use only; avoid contact with eyes.

Ask a doctor before use if you have cough associated with
smoking
excessive phlegm
asthma
emphysema
persistent or chronic cough

When using this product

Do not heat
microwave
add to hot water or any container where healing water may cause splattering and result in burns
use in eyes or directly on mucous membranes
take by mouth or place in nostrils
apply to wounds or damaged skin.
bandage skin.

Consult a doctor and discontinue use;
if condition worsens, persists for more than 1 week or tends to recur.

Keep out of reach of children.

In case of accidental ingestion, seek professional assistance or contact a Poison Control Center immediately

Directions

For the temporary relief of minor muscle aches and pains.
See important warnings under "When Using This Product"
not for use on children under 2 years of age
adults and children 2 y ears and older: apply liberally to painful area and massage until gel is absorbed into the skin. Repeat 3 to 4 times daily.

INACTIVE INGREDIENT

Inactive Ingredients: Camphor, Carbomer, FDandC Blue No1, Isopropyl Alcohol, methylchloroisothiazolinone, methylisothiazolinone, Sodium hydroxide, water.

PACKAGE LABEL

DT ICE COLD
ANALGSIC GEL
Distributed by:
DT products
Vernon,CA 90058
MADE IN CHINA